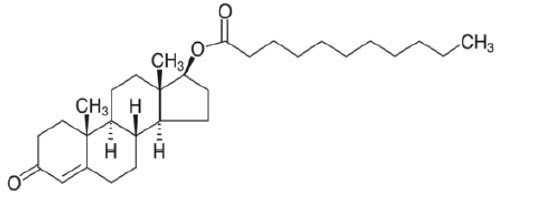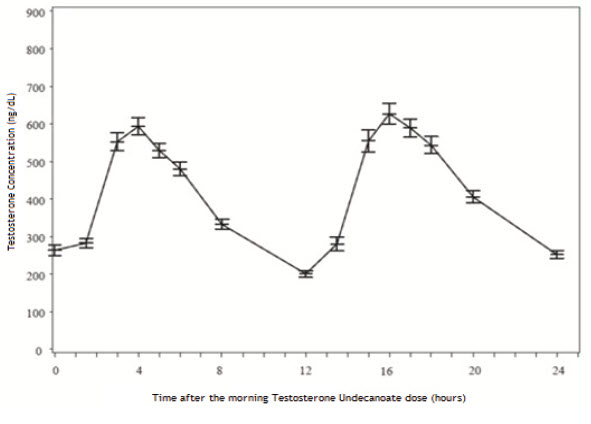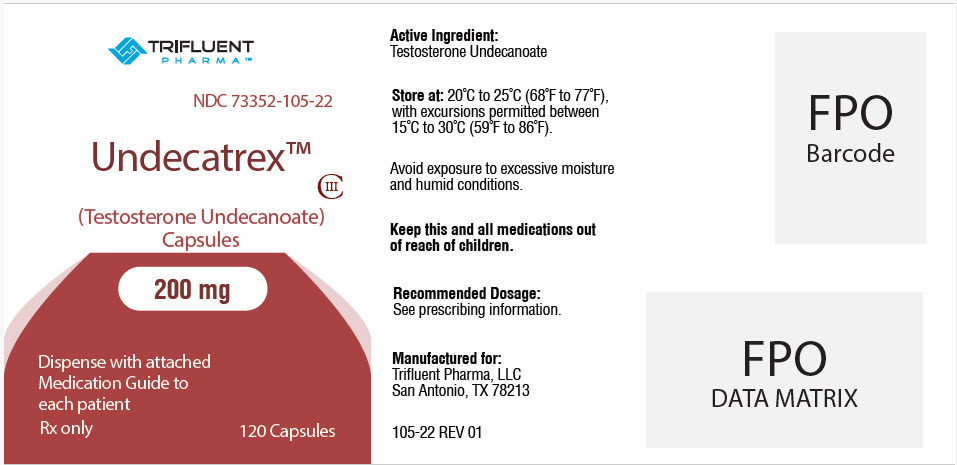 DRUG LABEL: Undecatrex
NDC: 73352-105 | Form: CAPSULE
Manufacturer: Trifluent Pharma LLC
Category: prescription | Type: HUMAN PRESCRIPTION DRUG LABEL
Date: 20220901
DEA Schedule: CIII

ACTIVE INGREDIENTS: TESTOSTERONE UNDECANOATE 200 mg/1 1
INACTIVE INGREDIENTS: POLYOXYL 40 HYDROGENATED CASTOR OIL; .ALPHA.-TOCOPHEROL; GELATIN, UNSPECIFIED; SORBITOL; GLYCERIN; WATER; TITANIUM DIOXIDE; PROPYLENE GLYCOL MONOLAURATE

HIGHLIGHTS OF PRESCRIBING INFORMATION

These highlights do not include all the information needed to use Testosterone Undecanoate Capsules safely and effectively. See full prescribing information for Testosterone Undecanoate Capsules.
Testosterone Undecanoate Capsules (testosterone undecanoate) capsules, for oral use, CIII
Initial U.S. approval: 1953

WARNING: BLOOD PRESSURE INCREASES

See full prescribing information for complete boxed warning

- Testosterone Undecanoate Capsules can cause blood pressure (BP) increases that can increase the risk of major adverse cardiovascular events (MACE), including non-fatal myocardial infarction, non-fatal stroke and cardiovascular death (5.1, 5.3, 6.1).
- Before initiating Testosterone Undecanoate Capsules, consider the patient's baseline cardiovascular risk and ensure blood pressure is adequately controlled (5.1, 5.3).
- Periodically monitor for and treat new-onset hypertension or exacerbations of pre-existing hypertension and re-evaluate whether the benefits of Testosterone Undecanoate Capsules outweigh its risks in patients who develop cardiovascular risk factors or cardiovascular disease on treatment (5.1, 5.3).
- Due to this risk, use Testosterone Undecanoate Capsules only for the treatment of men with hypogonadal conditions associated with structural or genetic etiologies (1, 4).

1 INDICATIONS AND USAGE

Testosterone Undecanoate Capsules is an androgen indicated for testosterone replacement therapy in adult males for conditions associated with a deficiency or absence of endogenous testosterone (1).
Limitations of Use:

- Safety and efficacy of Testosterone Undecanoate Capsules in males less than 18 years old have not been established (1, 8.4).

2 DOSAGE AND ADMINISTRATION

- Testosterone Undecanoate Capsules is not substitutable with other oral testosterone undecanoate products (2.1).
- Prior to initiating Testosterone Undecanoate Capsules, confirm the diagnosis of hypogonadism by ensuring that serum testosterone concentrations have been measured in the morning on at least two separate days and that these concentrations are below the normal range (2.2).
- Take Testosterone Undecanoate Capsules with food (2.3).
- Starting dosage: 200 mg orally once in the morning and once in the evening (2.3).
- Adjust the dosage to a minimum of 100 mg once in the morning and a maximum of 400 mg twice daily based on serum testosterone drawn 3 to 5 hours after the morning dose at least 7 days after starting treatment or following dose adjustment and periodically thereafter (2.3).

3 DOSAGE FORMS AND STRENGTHS

Capsules: 100 mg, 150 mg, 200 mg (3).

4 CONTRAINDICATIONS

- Carcinoma of the breast or known or suspected carcinoma of the prostate (5.4)
- Women who are pregnant. Testosterone may cause fetal harm (4, 5.7, 8.1)
- Hypersensitivity to Testosterone Undecanoate Capsules or any of its ingredients (4)
- Hypogonadal conditions not associated with structural or genetic etiologies (4)

5 WARNINGS AND PRECAUTIONS

- Polycythemia: Monitor hemoglobin or hematocrit approximately every 3 months to detect increased red blood cell mass and polycythemia. Discontinue Testosterone Undecanoate Capsules if necessary (5.2).
- Worsening of Benign Prostatic Hyperplasia (BPH) and Potential Risk of Prostate Cancer: Monitor patients for worsening of signs and symptoms of BPH. Evaluate patients for prostate cancer, including monitoring prostate specific antigen (PSA) prior to initiating and during treatment with androgens (5.4).
- Venous thromboembolism (VTE): VTE, including deep vein thrombosis (DVT) and pulmonary embolism (PE) have been reported in patients using testosterone. Discontinue Testosterone Undecanoate Capsules if VTE is suspected and initiate appropriate workup and management (5.5).
- Abuse of Testosterone and Monitoring of Serum Testosterone: If testosterone use at doses higher than recommended for the approved indication and in combination with other anabolic androgenic steroids is suspected, check serum testosterone concentration (5.6).
- Potential for Adverse Effects on Spermatogenesis: Testosterone Undecanoate Capsules may cause azoospermia (5.8).
- Edema: Edema, with or without congestive heart failure (CHF), may occur in patients with pre-existing cardiac, renal, or hepatic disease. Discontinue Testosterone Undecanoate Capsules and initiate appropriate workup (5.10).
- Sleep Apnea: Testosterone Undecanoate Capsules may potentiate sleep apnea in those with risk factors (5.11)
- Lipid Changes: Testosterone Undecanoate Capsules may affect serum lipid profile. Monitor patient lipid concentrations periodically; if necessary, adjust dosage of lipid lowering drug(s) or discontinue Testosterone Undecanoate Capsules (5.13).

6 ADVERSE REACTIONS

Most common adverse reactions (incidence ≥ 2%): hypertension (6.1).

To report SUSPECTED ADVERSE REACTIONS, contact Trifluent Pharma at 210-944-6920 or FDA at 1-800-FDA-1088 or www.fda.gov/medwatch.

7 DRUG INTERACTIONS

- Insulin: In patients with diabetes, concomitant use with Testosterone Undecanoate Capsules may decrease blood glucose and insulin requirements (7.1).
- Oral Anticoagulants: Concomitant use with Testosterone Undecanoate Capsules may cause changes in anticoagulant activity. Monitor International Normalized Ratio (INR) and prothrombin time (PT) frequently (7.2).
- Corticosteroids: Concomitant use with Testosterone Undecanoate Capsules may result in increased fluid retention. Use with caution, particularly in patients with cardiac, renal, or hepatic disease (7.3).
- Drugs that May Also Increase Blood Pressure: Concomitant use with Testosterone Undecanoate Capsules may lead to additional increases in blood pressure (7.4).

8 USE IN SPECIFIC POPULATIONS

Geriatric Patients: Geriatric patients treated with androgens may also be at risk for worsening of signs and symptoms of BPH and hypertension (8.5).

FULL PRESCRIBING INFORMATION

WARNING: BLOOD PRESSURE INCREASES

- Testosterone Undecanoate Capsules can cause blood pressure (BP) increases that can increase the risk of major adverse cardiovascular events (MACE), including non-fatal myocardial infarction, non-fatal stroke and cardiovascular death, with greater risk for MACE in patients with cardiovascular risk factors or established cardiovascular disease [see Warnings and Precautions (5.1, 5.3) and Adverse Reactions (6.1)].
- Before initiating Testosterone Undecanoate Capsules, consider the patient's baseline cardiovascular risk and ensure blood pressure is adequately controlled [see Warnings and Precautions (5.3)].
- After initiating therapy, periodically monitor for and treat new-onset hypertension or exacerbations of pre-existing hypertension [see Warnings and Precautions (5.1)].
- Re-evaluate whether the benefits of Testosterone Undecanoate Capsules outweigh its risks in patients who develop cardiovascular risk factors or cardiovascular disease while on treatment [see Warnings and Precautions (5.3)].
- Due to this risk, use Testosterone Undecanoate Capsules only for the treatment of men with hypogonadal conditions associated with structural or genetic etiologies [see Indications and Usage (1) and Contraindications (4)].

1 INDICATIONS AND USAGE

Testosterone Undecanoate Capsules is indicated for testosterone replacement therapy in adult males for conditions associated with a deficiency or absence of endogenous testosterone:

- Primary hypogonadism (congenital or acquired): testicular failure due to conditions such as cryptorchidism, bilateral torsion, orchitis, vanishing testis syndrome, orchiectomy, Klinefelter syndrome, chemotherapy, or toxic damage from alcohol or heavy metals. These men usually have low serum testosterone concentrations and gonadotropins (follicle stimulating hormone (FSH), luteinizing hormone (LH) above the normal range.
- Hypogonadotropic hypogonadism (congenital or acquired): gonadotropin or luteinizing hormone-releasing hormone (LHRH) deficiency, pituitary-hypothalamic injury from tumors, trauma, or radiation. These men have low serum testosterone concentrations but have gonadotropins in the normal or low range.

Limitations of Use

Safety and efficacy of Testosterone Undecanoate Capsules in males less than 18 years old have not been established [see Use in Specific Populations (8.4)].

2 DOSAGE AND ADMINISTRATION

2.1 Important Dosage Information

Testosterone Undecanoate Capsules is not substitutable with other oral testosterone undecanoate products.

2.2 Confirmation of Hypogonadism Before Initiation of Testosterone Undecanoate Capsules

Prior to initiating Testosterone Undecanoate Capsules, confirm the diagnosis of hypogonadism by ensuring that serum testosterone concentrations have been measured in the morning on at least two separate days and that these testosterone concentrations are below the normal range.

2.3 Recommended Dosage and Administration

Individualize the dosage of Testosterone Undecanoate Capsules based on the patient's serum testosterone concentration response to the drug.

The recommended starting dose is 200 mg orally twice daily, once in the morning and once in the evening. Take Testosterone Undecanoate Capsules with food.

Dosage Adjustment

Check serum testosterone concentrations 7 days after starting treatment or after dosage adjustment, 3 to 5 hours after the morning dose. Adjust the Testosterone Undecanoate Capsules dose as necessary as shown in Table 1. Thereafter, periodically monitor serum testosterone concentrations.

The minimum recommended dose is 100 mg once daily in the morning. The maximum recommended dose is 400 mg twice daily. For total daily doses greater than 100 mg, administer the same dose in the morning and evening.

Table 1: Testosterone Undecanoate Capsules Dosage Adjustment Scheme
Serum Testosterone Concentration | Current Testosterone Undecanoate Capsules Dosage | New Testosterone Undecanoate Capsules Dosage
Less than 460 ng/dL | 100 mg with breakfast only | 100 mg twice daily with meals
Less than 460 ng/dL | 100 mg twice daily with meals | 200 mg twice daily with meals
Less than 460 ng/dL | 200 mg twice daily with meals | 300 mg twice daily with meals
Less than 460 ng/dL | 300 mg twice daily with meals | 400 mg twice daily with meals
460 to 971 ng/dL | No Dosage Change
More than 971 ng/dL | 400 mg twice daily with meals | 300 mg twice daily with meals
More than 971 ng/dL | 300 mg twice daily with meals | 200 mg twice daily with meals
More than 971 ng/dL | 200 mg twice daily with meals | 100 mg twice daily with meals
More than 971 ng/dL | 100 mg twice daily with meals | 100 mg with breakfast only
More than 971 ng/dL | 100 mg with breakfast only | Discontinue treatment

3 DOSAGE FORMS AND STRENGTHS

Capsules:

- 100 mg, oval, opaque, white, imprinted with "MP100" in red ink
- 150 mg, oblong, opaque, white, imprinted with "MP150" in red ink
- 200 mg, oblong, opaque, white, imprinted with "MP200" in red ink

4 CONTRAINDICATIONS

Testosterone Undecanoate Capsules is contraindicated in:

- Patients with carcinoma of the breast or known or suspected carcinoma of the prostate [see Warnings and Precautions (5.4)].
- Women who are pregnant. Testosterone can cause virilization of the female fetus when administered to a pregnant woman [see Use in Specific Populations (8.1)].
- Patients with known hypersensitivity to Testosterone Undecanoate Capsules or any of its ingredients [see Description (11)].
- Men with hypogonadal conditions, such as "age-related hypogonadism," that are not associated with structural or genetic etiologies. The efficacy of Testosterone Undecanoate Capsules has not been established for these conditions, and Testosterone Undecanoate Capsules can increase BP that can increase the risk of MACE [see Boxed Warning and Warning and Precautions (5.1)].

5 WARNINGS AND PRECAUTIONS

5.1 Increase in Blood Pressure

In Study MRS-TU-2019EXT, Testosterone Undecanoate Capsules increased 24-hour average systolic blood pressure (SBP) measured by ambulatory blood pressure monitoring (ABPM) by 1.7 mmHg from baseline after 4 months of treatment and 1.8 mmHg from baseline after 6 months of treatment [see Adverse Reactions (6.1)] . Three percent of Testosterone Undecanoate Capsules treated patients were started on antihypertensive medications during the 6-month trial.

A history of antihypertensive treatment and diabetes mellitus at baseline were significant factors related to ambulatory SBP increases [see Adverse Reactions (6.1)].

Blood pressure (BP) increases can increase the risk of major adverse cardiovascular events (MACE), with greater risk in patients with established cardiovascular disease or risk factors for cardiovascular disease. In some patients, the increase in BP with Testosterone Undecanoate Capsules may be too small to detect but can still increase the risk for MACE.

Before initiating Testosterone Undecanoate Capsules, consider the patient's baseline cardiovascular risk and ensure blood pressure is adequately controlled. Check BP periodically after initiating Testosterone Undecanoate Capsules or increasing the dose and thereafter. Treat new-onset hypertension or exacerbations of pre-existing hypertension. Re-evaluate whether the benefits of continued treatment with Testosterone Undecanoate Capsules outweigh its risks in patients who develop cardiovascular risk factors or cardiovascular disease.

5.2 Polycythemia

Androgens, including Testosterone Undecanoate Capsules, can cause increase in hemoglobin or hematocrit, reflective of increase in red blood cell mass. Check hematocrit prior to initiating Testosterone Undecanoate Capsules. An increase in red blood cell mass may increase the risk of thromboembolic events [see Warnings and Precautions (5.5)]. Evaluate hematocrit approximately every 3 months while the patient is on Testosterone Undecanoate Capsules. If hematocrit becomes elevated, stop Testosterone Undecanoate Capsules until the hematocrit decreases to an acceptable concentration. If Testosterone Undecanoate Capsules is restarted and again causes hematocrit to become elevated, permanently discontinue Testosterone Undecanoate Capsules.

5.3 Cardiovascular Risk

Long-term clinical safety trials have not been conducted to assess the cardiovascular outcomes of testosterone replacement therapy in men. To date, epidemiologic studies and randomized controlled trials have been inconclusive for determining the risk of MACE, such as non-fatal myocardial infarction, non-fatal stroke, and cardiovascular death, with testosterone use compared to non-use. Some studies have reported an increased risk of MACE in association with use of testosterone replacement therapy in men.

Testosterone Undecanoate Capsules can cause BP increases that can increase the risk of MACE [see Warnings and Precautions (5.1)]. Patients should be informed of this possible risk when deciding whether to use or to continue to use Testosterone Undecanoate Capsules.

5.4 Worsening of Benign Prostatic Hyperplasia (BPH) and Potential Risk of Prostate Cancer

- Patients with BPH who are treated with androgens are at an increased risk for worsening of signs and symptoms of BPH. Monitor patients with BPH for worsening signs and symptoms.
- Patients treated with androgens may be at increased risk for prostate cancer. Evaluate patients for prostate cancer prior to initiating and during treatment with androgens [see Contraindications (4)].

5.5 Venous Thromboembolism

There have been post-marketing reports of venous thromboembolic events, including deep vein thrombosis (DVT) and pulmonary embolism (PE), in patients using testosterone replacement products such as Testosterone Undecanoate Capsules. Evaluate patients who report symptoms of pain, edema, warmth, and erythema in the lower extremity for DVT and those who present with acute shortness of breath for PE. If a venous thromboembolic event is suspected, discontinue Testosterone Undecanoate Capsules and initiate appropriate workup and management [see Adverse Reactions (6.2)].

5.6 Abuse of Testosterone and Monitoring of Testosterone Concentrations

Testosterone has been subject to abuse, typically at doses higher than recommended for the approved indication and in combination with other anabolic androgenic steroids. Anabolic androgenic steroid abuse can lead to serious cardiovascular and psychiatric adverse reactions [see Drug Abuse and Dependence (9)].

If testosterone abuse is suspected, check testosterone concentrations to ensure they are within therapeutic range [see Dosage and Administration (2.2)]. Testosterone levels may remain in the normal or subnormal range in men abusing synthetic testosterone derivatives. Counsel patients concerning the serious adverse reactions associated with abuse of testosterone and anabolic androgenic steroids. Also consider the possibility of testosterone and anabolic androgenic steroid abuse in suspected patients who present with serious cardiovascular or psychiatric adverse events.

5.7 Not for Use in Women

Due to lack of controlled studies in women and potential virilizing effects,Testosterone Undecanoate Capsules is not indicated for use in women [see Contraindications (4) and Use in Specific Populations (8.1, 8.2)].

5.8 Potential for Adverse Effects on Spermatogenesis

With large doses of exogenous androgens, including Testosterone Undecanoate Capsules, spermatogenesis may be suppressed through feedback inhibition of pituitary FSH, possibly leading to adverse effects on semen parameters including sperm count [see Use in Specific Populations (8.3)]. Inform patients of this possible risk when deciding whether to use or to continue to use Testosterone Undecanoate Capsules.

5.9 Hepatic Adverse Effects

Testosterone Undecanoate is not a 17-alpha-alkyl androgen and is not known to cause hepatic adverse effects. However, prolonged use of high doses of orally active 17-alpha-alkyl androgens (e.g., methyltestosterone) has been associated with serious hepatic adverse effects (peliosis hepatis, hepatic neoplasms, cholestatic hepatitis, and jaundice). Peliosis hepatis can be a life-threatening or fatal complication. Long-term therapy with intramuscular testosterone enanthate has produced multiple hepatic adenomas. Patients should be instructed to report any signs or symptoms of hepatic dysfunction (e.g., jaundice). If these occur, promptly discontinue Testosterone Undecanoate Capsules while the cause is evaluated.

5.10 Edema

Androgens, including Testosterone Undecanoate, may promote retention of sodium and water. Edema, with or without congestive heart failure, may be a serious complication in patients with pre-existing cardiac, renal, or hepatic disease [see Adverse Reactions (6.1)]. In addition to discontinuation of the drug, diuretic therapy may be required.

5.11 Sleep Apnea

The treatment of hypogonadal men with testosterone may potentiate sleep apnea in some patients, especially those with risk factors such as obesity or chronic lung disease.

5.12 Gynecomastia

Gynecomastia may develop and persist in patients being treated for hypogonadism.

5.13 Lipid Changes

In clinical trials, patients receiving Testosterone Undecanoate Capsules experienced reductions in lipid parameters, including total cholesterol, LDL cholesterol, HDL cholesterol, and triglycerides [see Adverse Reactions (6.1)]. Changes in the serum lipid profile may require dose adjustment of lipid lowering drugs or discontinuation of testosterone therapy. Monitor the lipid profile periodically, particularly after starting testosterone therapy.

5.14 Hypercalcemia

Androgens, including Testosterone Undecanoate, should be used with caution in cancer patients at risk of hypercalcemia (and associated hypercalciuria). Monitor serum calcium concentrations periodically during treatment with Testosterone Undecanoate Capsules in these patients.

5.15 Decreased Thyroxine-binding Globulin

Androgens, including Testosterone Undecanoate, may decrease concentrations of thyroxin-binding globulin, resulting in decreased total T4 serum concentrations and increased resin uptake of T3 and T4. Free thyroid hormone concentrations remain unchanged, however, and there is no clinical evidence of thyroid dysfunction.

6 ADVERSE REACTIONS

The following clinically significant adverse reactions are discussed elsewhere in the labeling:

- Increase in Blood Pressure [see Warnings and Precautions (5.1)]
- Polycythemia [see Warnings and Precautions (5.2)]
- Cardiovascular Risk [see Warnings and Precautions (5.3)]
- Worsening of Benign Prostatic Hyperplasia (BPH) and Potential Risk of Prostate Cancer [see Warnings and Precautions (5.4)]
- Venous Thromboembolism [see Warnings and Precautions (5.5)]
- Hepatic Adverse Effects [see Warnings and Precautions (5.9)]
- Edema [see Warnings and Precautions (5.10)]
- Sleep Apnea [see Warnings and Precautions (5.11)]
- Gynecomastia [see Warnings and Precautions (5.12)]
- Lipid Changes [see Warnings and Precautions (5.13)]
- Hypercalcemia [see Warnings and Precautions (5.14)]
- Decreased Thyroxine-binding Globulin [see Warnings and Precautions (5.15)]

6.1 Clinical Trial Experience

Because clinical trials are conducted under widely varying conditions, adverse reaction rates observed in the clinical trials of a drug cannot be directly compared to rates in the clinical trials of another drug and may not reflect the rates observed in practice.

The safety of Testosterone Undecanoate Capsules was evaluated in Study MRS-TU-2019EXT in 155 hypogonadal males [see Clinical Studies (14)]. All patients initially received Testosterone Undecanoate Capsules 200 mg orally twice daily. If needed, the dosage was titrated to 100 mg once daily in the morning or 100 mg, 300 mg, or 400 mg twice daily to achieve testosterone concentrations in the normal range. After the dosage titration period, patients continued their optimized dose for the remainder of the duration of the 6-month study. The mean duration of exposure was 168 days (range: 1 to 180 days). The median age was 52 years (range: 22 to 66 years); 77% were White, 19% were Black, 3% were Asian, and 2% were American Indian, Alaskan Native or Other.

Table 2 summarizes adverse reactions reported in ≥ 2% of patients in this 6-month study.

Table 2: Adverse Reactions in ≥ 2% of Patients Receiving Testosterone Undecanoate Capsules in STUDY MRS-TU-2019EXT
Adverse Reaction | N = 155 n (%)
Hypertensión [Based upon blood pressure cuff measurements] | 4 (2.6)

One (0.8%) patient who received of Testosterone Undecanoate Capsules experienced an adverse reaction (acne) that lead to premature discontinuation from the study.

In a 12-month, open-label study in hypogonadal adult males (N=212) who received of Testosterone Undecanoate Capsules 200 mg once daily to 400 mg twice daily (n=202) the following additional adverse reactions were reported: headache, arthralgia, diarrhea, hemoglobin increased, anxiety, constipation, peripheral edema, and PSA increased.

Blood Pressure Increases

Ambulatory (24-hour) and in-clinic (cuff) blood pressure Changes from Baseline for study MRS-TU-2019EXT are presented in Table 3 with 95% confidence intervals. No significant difference was observed between the 4-month and 6-month Changes from Baseline.

Table 3: Blood Pressure Increases
Blood Pressure | Change from Baseline (95% CI) mm Hg
 | Systolic | Diastolic
24-Hour Ambulatory
4 Month | 1.7 (0.3 to 3.1) | 0.6 (-0.3 to 1.6)
6 Month | 1.8 (0.3 to 3.2) | 0.6 (-0.4 to 1.6)
In-clinic (blood pressure cuff)
4 Month | 2.7 (0.9 to 4.5) | 1.5 (0.3 to 2.6)
6 Month | 2.4 (0.6 to 4.2) | 1.7 (0.5 to 2.9)

A total of 5 of 155 patients (3.2%) in Study MRS-TU-2019EXT began taking new antihypertensive medications after study start. No patient had a dose increase in their antihypertensive medication by the end of treatment.

A history of antihypertensive treatment and diabetes mellitus at baseline were significant factors related to ambulatory SBP increases.

Table 4 presents the Least Squares Mean estimates of Change from Baseline, with 95% CI's, for sub-populations of subjects at study start either with or without hypertensive treatment or with or without diabetes mellitus.

Table 4: Ambulatory Blood Pressure Increases by Subject Sub-group
Subgroups | Ambulatory Systolic Blood Pressure Change from Baseline (95% CI), mm Hg
With hypertensive treatment at baseline (n=49)
4 Month | 3.4 (1.0 to 5.9)
6 Month | 3.1 (0.6 to 5.6)
Without hypertensive treatment at baseline (n=90)
4 Month | 0.7 (-1.0 to 2.4)
6 Month | 1.0 (-0.7 to 2.8)
With diabetes at baseline (n=29)
4 Month | 3.0 (-0.2 to 6.2)
6 Month | 3.4 (0.2 to 6.7)
Without diabetes at baseline (n=110)
4 Month | 1.3 (-0.2 to 2.9)
6 Month | 1.3 (-0.3 to 2.9)

Heart Rate Increases

Testosterone Undecanoate Capsules increased mean (95%CI) 24-hour ambulatory heart rate by an average of 0.7 (-0.5 to 1.9) beats per minute (bpm) at 4 months and 1.9 (0.6 to 3.1) bpm at 6 months in Study MRS-TU-2019EXT. Changes in heart rate were similar between patients with or without hypertension or diabetes. Changes in heart rate with treatment were most prominent in the evening, 12 to 17 hours after the morning dose.

Increases in Hemoglobin

Increases in hemoglobin were reported in 7 out of 155 patients (4.5%) in Study MRS- TU2019EXT. None of these increases led to premature discontinuation of Testosterone Undecanoate Capsules.

Hematocrit was not assessed in this study.

Headaches

Headaches were reported in 3 of 155 patients (1.9%) receiving Testosterone Undecanoate Capsules in Study MRSTU-2019EXT.

Increases in Serum PSA

Four out of 155 patients (2.6%) receiving Testosterone Undecanoate Capsules in Study MRS-TU-2019EXT had an increase in PSA from baseline greater than 1.4 ng/mL and two out of 155 patients (1.3%) had a PSA of at least 4.0 ng/mL during Study MRS-TU-2019EXT. The mean (SE) increase in PSA from baseline was 0.15 (±0.04) ng/mL at 6 months (n=135).

6.2 Postmarketing Experience

The following adverse reactions have been identified during post-approval use of testosterone. Because these reactions are reported voluntarily from a population of uncertain size, it is not always possible to reliably estimate their frequency or establish a causal relationship to drug exposure.

Cardiovascular Disorders: myocardial infarction, stroke
Vascular Disorders: Venous thromboembolism

7 DRUG INTERACTIONS

7.1 Insulin

Changes in insulin sensitivity or glycemic control may occur in patients treated with androgens. In diabetic patients, the metabolic effects of androgens may decrease blood glucose and therefore necessitate a decrease in the dose of anti-diabetic medication.

7.2 Oral Vitamin K Antagonist Anticoagulants

Changes in anticoagulant activity may be seen with androgens; therefore, more frequent monitoring of international normalized ratio (INR) and prothrombin time are recommended in patients taking warfarin, especially at the initiation and termination of androgen therapy.

7.3 Corticosteroids

The concurrent use of testosterone with corticosteroids may result in increased fluid retention and requires careful monitoring particularly in patients with cardiac, renal, or hepatic disease.

7.4 Medications that May Also Increase Blood Pressure

Some prescription medications and nonprescription analgesic and cold medications contain drugs known to increase blood pressure. Concomitant administration of these medications with Testosterone Undecanoate Capsules may lead to additional increases in blood pressure [see Warnings and Precautions (5.1)].

8 USE IN SPECIFIC POPULATIONS

8.1 Pregnancy

Risk Summary

Testosterone Undecanoate Capsules is contraindicated in pregnant women and not indicated for use in females [see Contraindications (4)]. Testosterone is teratogenic and may cause fetal harm when administered to a pregnant woman based on data from animal studies (see Data) and its mechanism of action [see Clinical Pharmacology (12.1)]. Exposure of a female fetus to androgens may result in varying degrees of virilization. In animal developmental studies, exposure to testosterone in utero resulted in hormonal and behavioral changes in offspring and structural impairments of reproductive tissues in female and male offspring. These studies do not meet current standards for nonclinical development toxicity studies.

Data

Animal Data

In developmental studies conducted in rats, rabbits, pigs, sheep, and rhesus monkeys, pregnant animals received intramuscular injections of testosterone during the period of organogenesis. Testosterone treatment at doses that were comparable to those used for testosterone replacement therapy resulted in structural impairments in both female and male offspring. Structural impairments observed in females included increased anogenital distance, phallus development, empty scrotum, no external vagina, intrauterine growth retardation, reduced ovarian reserve, and increased ovarian follicular recruitment. Structural impairments seen in male offspring included increased testicular weight, larger seminal tubular lumen diameter, and higher frequency of occluded tubule lumen. Increased pituitary weight was seen in both sexes.

Testosterone exposure in utero also resulted in hormonal and behavioral changes in offspring. Hypertension was observed in pregnant female rats and their offspring exposed to doses approximately twice those used for testosterone replacement therapy.

8.2 Lactation

Risk Summary

Testosterone Undecanoate Capsules is not indicated for use in females.

8.3 Females and Males of Reproductive Potential

Infertility

Males

During treatment with large doses of exogenous androgens, including Testosterone Undecanoate Capsules, spermatogenesis may be suppressed through feedback inhibition of the hypothalamic pituitary-testicular axis [see Warnings and Precautions (5.8) and Impairment of Fertility (13.1)], possibly leading to adverse effects on semen parameters including sperm count. Reduced fertility has been observed in some men taking testosterone replacement therapy. Testicular atrophy, subfertility, and infertility have also been reported in men who abuse anabolic androgenic steroids [see Drug Abuse and Dependence (9.2)]. With either type of use, the impact on fertility may be irreversible.

8.4 Pediatric Use

The safety and efficacy of Testosterone Undecanoate Capsules in pediatric patients less than 18 years old have not been established. Testosterone Undecanoate Capsules is not recommended for use in patients less than 18 years of age because of the potential for acceleration of bone age and premature closure of epiphyses.

8.5 Geriatric Use

Clinical studies of Testosterone Undecanoate Capsules did not include any patients 65 years of age and older. Therefore, it cannot be determined whether these patients respond differently from younger adult patients. Additionally, there are insufficient long-term safety data in geriatric patients to assess the potentially increased risk of cardiovascular disease and prostate cancer.

Geriatric patients treated with androgens including Testosterone Undecanoate Capsules may be at risk for worsening of signs and symptoms of BPH [see Warnings and Precautions (5.4)].

9 DRUG ABUSE AND DEPENDENCE

9.1 Controlled Substance

Testosterone Undecanoate Capsules contains testosterone undecanoate, a Schedule III controlled substance

9.2 Abuse

Drug abuse is intentional non-therapeutic use of a drug, even once, for its rewarding psychological and physiological effects. Abuse and misuse of testosterone are seen in male and female adults and adolescents. Testosterone, often in combination with other anabolic androgenic steroids, and not obtained by prescription through a pharmacy, may be abused by athletes and bodybuilders. There have been reports of misuse by men taking higher doses of legally obtained testosterone than prescribed and continuing testosterone despite adverse events or against medical advice.

Abuse-Related Adverse Reactions

Serious adverse reactions have been reported in individuals who abuse anabolic androgenic steroids and include cardiac arrest, myocardial infarction, hypertrophic cardiomyopathy, congestive heart failure, cerebrovascular accident, hepatotoxicity, and serious psychiatric manifestations, including major depression, mania, paranoia, psychosis, delusions, hallucinations, hostility, and aggression.

The following adverse reactions have also been reported in men: transient ischemic attacks, convulsions, hypomania, irritability, dyslipidemias, testicular atrophy, subfertility, and infertility.

The following additional adverse reactions have been reported in women: hirsutism, virilization, deepening of voice, clitoral enlargement, breast atrophy, male-pattern baldness, and menstrual irregularities. The following adverse reactions have been reported in male and female adolescents: premature closure of bony epiphyses with termination of growth, and precocious puberty.

Because these reactions are reported voluntarily from a population of uncertain size and may include abuse of other agents, it is not always possible to reliably estimate their frequency or establish a causal relationship to drug exposure.

9.3 Dependence

Behaviors Associated with Addiction

Continued abuse of testosterone and other anabolic steroids leading to addiction is characterized by the following behaviors:

- Taking greater dosages than prescribed
- Continued drug use despite medical and social problems due to drug use
- Spending significant time to obtain the drug when supplies of the drug are interrupted
- Giving a higher priority to drug use than other obligations
- Having difficulty in discontinuing the drug despite desires and attempts to do so
- Experiencing withdrawal symptoms upon abrupt discontinuation of use

Physical dependence is characterized by withdrawal symptoms after abrupt drug discontinuation or a significant dose reduction of a drug. Individuals taking supratherapeutic doses of testosterone may experience withdrawal symptoms lasting for weeks or months, which may include depressed mood, major depression, fatigue, craving, restlessness, irritability, anorexia, insomnia, decreased libido, and hypogonadotropic hypogonadism.

Drug dependence in individuals using approved doses of testosterone for approved indications has not been documented.

10 OVERDOSAGE

There is one report of acute overdosage with use of an approved injectable testosterone product: this subject had serum testosterone levels of up to 11,400 ng/dL with a cerebrovascular accident.

Treatment of overdosage consists of discontinuation of Testosterone Undecanoate Capsules and appropriate symptomatic and supportive care.

11 DESCRIPTION

Testosterone Undecanoate Capsules is provided as a gelatin capsule containing testosterone undecanoate, a fatty-acid ester of testosterone. Testosterone undecanoate is a white to off-white yellow crystalline powder. Testosterone, an androgen, is formed by cleavage of the ester side chain of testosterone undecanoate.

Testosterone undecanoate is chemically described as 17β-hydroxyandrost-4-en-3-one undecanoate. It has the empirical formula of C30H48O3 and a molecular weight of 456.7 g/mol. The structural formula for testosterone undecanoate is presented in Figure 1.

Figure 1: Testosterone Undecanoate

Testosterone Undecanoate Capsules (testosterone undecanoate) capsules for oral use are available in three dosage strengths- 100 mg, 150 mg, and 200 mg. The 100 mg strength is an opaque, white capsule imprinted with "MP100" in red ink. The 150 mg strength is an opaque white capsule imprinted with "MP150" in red ink. The 200 mg strength is an opaque white capsule imprinted with "MP200" in red ink. All capsule strengths also contain DL-alpha- tocopheryl acetate (Vitamin E), phytosterol esters, polyoxyl 40 hydrogenated castor oil, and propylene glycol monolaurate as inactive ingredients.

Gelatin capsule shells are composed of the following inactive ingredients: gelatin, glycerin, purified water, sorbitol, and titanium dioxide.

12 CLINICAL PHARMACOLOGY

12.1 Mechanism of Action

Endogenous androgens, including testosterone and dihydrotestosterone (DHT), are responsible for the normal growth and development of the male sex organs and for maintenance of secondary sex characteristics. These effects include the growth and maturation of prostate, seminal vesicles, penis, and scrotum; the development of male hair distribution, such as facial, pubic, chest, and axillary hair; laryngeal enlargement; vocal cord thickening; alterations in body musculature; and fat distribution.

Male hypogonadism, a clinical syndrome resulting from insufficient secretion of testosterone, has two main etiologies. Primary hypogonadism is caused by defects of the gonads, such as Klinefelter syndrome or Leydig cell aplasia, whereas secondary hypogonadism (also known as hypogonadotropic hypogonadism) is the failure of the hypothalamus (or pituitary gland) to produce sufficient gonadotropins (FSH, LH).

12.2 Pharmacodynamics

There is insufficient data to characterize an exposure-response relationship or time course of pharmacodynamics.

12.3 Pharmacokinetics

Absorption

Testosterone Undecanoate Capsules was taken orally at a starting dose of 200 mg twice per day with meals in a multicenter, open-label trial in hypogonadal males. The dose was adjusted, as needed, on Days 28 and 56 from a minimum dose of 100 mg (morning-only) to a maximum dose of 400 mg twice per day based on the plasma testosterone concentration obtained by a single blood draw collected 3 to 5 hours after the morning dose. The average daily NaF/EDTA plasma testosterone concentration was 393.3 (±113.6) ng/dL after 90 days of treatment (normal eugonadal range in NaF/EDTA plasma: 222-800 ng/dL. Note that the titration scheme for use in clinical practice is based on serum total testosterone [see Dosage and Administration (2.2)].

Testosterone Undecanoate Capsules is expected to produce testosterone concentrations that approximate normal concentrations seen in healthy men.

Table 5 summarizes the pharmacokinetic (PK) parameters for plasma total testosterone in patients completing at least 90 days of Testosterone Undecanoate Capsules treatment administered daily.

Table 5: NaF-EDTA Plasma Testosterone C avg and C max at Day 90 Visit
PK Parameter |  | Plasma (N=130)
C avg (ng/dL) | n | 127
C avg (ng/dL) | Mean | 393.3
C avg (ng/dL) | SD | 113.6
C max (ng/dL) | n | 130
C max (ng/dL) | Mean | 852.4
C max (ng/dL) | SD | 311.3

PK = pharmacokinetic; C avg = 24-hour average concentration; C max = maximum concentration

Figure 2 summarizes the mean plasma total testosterone profile at the final PK visit.

Figure 2: Mean (±SEM) Concentration-Time Profile for NaF-EDTA Plasma Total Testosterone in Testosterone Undecanoate Capsules-Treated Patients at Day 90 Visit

SEM = standard error of the mean
Testosterone normal ranges: plasma = 222-800 ng/dL

When Testosterone Undecanoate [Capsules] was given with breakfast containing 16%, 33%, and 45% fat, the exposure (AUC 0-24 hr) of testosterone was increased by 37%, 87%, and 94%, respectively, compared to when given under fasted conditions. The primary efficacy and safety study was conducted under fed conditions regardless of the type of meals and the primary efficacy endpoint of achieving testosterone C avg in normal testosterone range was met.

There was no effect on testosterone PK when Testosterone Undecanoate [Capsules] was administered with 20% alcohol along with a high-fat meal versus a high-fat meal alone.

Distribution

Circulating testosterone is primarily bound in serum to sex hormone-binding globulin (SHBG) and albumin. Approximately 40% of testosterone in plasma is bound to SHBG, 2% remains unbound (free), and the rest is loosely bound to albumin and other proteins.

Metabolism

The androgenic activity of testosterone undecanoate occurs after the ester bond linking the testosterone to the undecanoic acid is cleaved by endogenous non-specific esterases. Undecanoic acid is metabolized like all fatty acids via the beta-oxidation pathway. Testosterone is metabolized to various 17-keto steroids through two different pathways. The major active metabolites of testosterone are dihydrotestosterone (DHT) and estradiol.

Excretion

About 90% of a dose of testosterone given intramuscularly is excreted in the urine as glucuronic and sulfuric acid conjugates of testosterone and its metabolites. About 6% of a dose is excreted in the feces, mostly in the unconjugated form. Inactivation of testosterone occurs primarily in the liver.

13 NONCLINICAL TOXICOLOGY

13.1 Carcinogenesis, Mutagenesis, Impairment of Fertility

Carcinogenesis

Testosterone has been tested by subcutaneous injection and implantation in mice and rats. In mice, the implant induced cervical-uterine tumors, which metastasized in some cases. There is suggestive evidence that injection of testosterone into some strains of female mice increases their susceptibility to hepatoma. Testosterone is also known to increase the number of tumors and decrease the degree of differentiation of chemically induced carcinomas of the liver in rats.

Mutagenesis

Testosterone was negative in the in vitro Ames and in the in vivo mouse micronucleus assays.

Impairment of Fertility

The administration of exogenous testosterone suppressed spermatogenesis and impaired fertility in the rat, dog, and non-human primate, which was reversible on cessation of treatment.

A reproductive toxicology study was conducted in rats to evaluate functional effects of Testosterone Undecanoate [Capsules] on male fertility. In untreated female rats mated with males receiving 2 times the maximum recommended human daily dose (MRHDD) of Testosterone Undecanoate [Capsules] (based on mean AUC exposure to testosterone), the number of impregnated females was reduced, fertility was significantly lower, and pre-implantation loss was significantly higher compared to the control group. There was no impairment of fertility in males receiving an equivalent dose of Testosterone Undecanoate [Capsules] to the MRHDD.

13.2 Animal Toxicology and/or Pharmacology

A 3-month repeat-dose oral toxicity study in male eugonadal dogs was conducted to evaluate whether phytosterol esters present in the Testosterone Undecanoate Capsules formulation influenced target organ toxicity due to their structural similarities to sex steroids like testosterone. Testosterone Undecanoate Capsules doses 2 times the MRHDD (based on mean AUC exposure to testosterone) produced similar effects on androgen-responsive tissues as testosterone undecanoate without phytosterol esters. These included mild to marked effects on the testes (decreased size, germ cell depletion, Leydig cell atrophy), epididymides (aspermia), adrenal glands (vacuolation in the zona fasciculata) and prostate (increased size and glandular hypertrophy/hyperplasia). Following a 4-week treatment-free period, findings in the testes, epididymides, and adrenal glands were not fully reversible at doses of 2 times the MRHDD of Testosterone Undecanoate Capsules as compared to treatment with the excipients alone, including phytosterol esters. Reversibility was not assessed in testosterone undecanoate groups without phytosterol esters.

14 CLINICAL STUDIES

The efficacy and safety of Testosterone Undecanoate Capsules were evaluated in Study MRS-TU-2019EXT (NCT04467697) a multi-center, open-label study of approximately 6 months of duration in 155 hypogonadal males.

Patients received Testosterone Undecanoate Capsules at a starting dose of 200 mg twice daily with meals. The dosage was adjusted on Days 28 and 56 between a minimum dose of 100 mg (single morning dose) and a maximum dose of 800 mg (400 mg twice daily) based on plasma testosterone concentration from a single blood draw between 3 to 5 hours after the morning dose.

The primary efficacy endpoint was the percentage of Testosterone Undecanoate Capsules-treated patients with mean plasma total testosterone concentration (C avg) over 24-hours within the normal range of 222-800 ng/dL on the final PK visit of the study at Day 90.

The efficacy population consisted of 139 hypogonadal, males with a median age of 50 years (range 22 to 66 years), 79% were White, 16% were Black, 3% were Asian, and 2% were American Indian, Alaskan Native or Other.

Primary efficacy results are summarized in Table 6.

Table 6: Proportion of Patients in Study MRS-TU-2019EXT with Average Plasma Total Testosterone in the Normal Range (222-800 ng/dL) on Day 90
Parameter | N=139
Patients (%) with Testosterone, C avg (ng/dL), 222-800 ng/dL | 122 (88%)
95% Confidence Interval | (82%, 93%)
C avg = 24-hour average concentration

Secondary endpoints were the percentage of patients with a maximum total testosterone concentration (C max) meeting three predetermined limits: less than or equal to 1.5 times the upper limit of normal range (ULN) (1200 ng/dL), between 1.8 and 2.5 times ULN (1440-2000 ng/dL), and greater than 2.5 times ULN (2000 ng/dL).

The percentage of patients who received Testosterone Undecanoate Capsules and had testosterone C max threshold less than or equal to 1200 ng/dL, between 1440 and 2000 ng/dL, and greater than 2000 ng/dL at the final PK visit were 88%, 4%, and 0%, respectively.

16 HOW SUPPLIED/STORAGE AND HANDLING

Undecatrex™ (Testosterone Undecanoate Capsules) are available in three strengths of 100 mg, 150 mg, and 200 mg. It is packaged in wide-mouth, round, white HDPE bottles with white, polypropylene, child resistant caps and induction-sealed liner.

100 mg: Oval, opaque, white capsules imprinted with "MP100" in red ink supplied in bottles; NDC 73352-101-22 for 120 capsules.

150 mg: Oblong, opaque, white capsules imprinted with "MP150" in red ink supplied in bottles; NDC 73352-103-22 for 120 capsules.

200 mg: Oblong, opaque, white capsules imprinted with "MP200" in red ink supplied in bottles; NDC 73352-105-22 for 120 capsules.

STORAGE AND HANDLING

Store at 20°C to 25°C (68°F to 77°F), with excursions permitted between 15°C to 30°C (59°F to 86°F) [see USP Controlled Room Temperature]. Store the capsules in a dry place avoiding exposure to excessive moisture and humid conditions.

Dispose of unused Testosterone Undecanoate Capsules via a take-back option. If a take-back option is unavailable, follow FDA instructions at www.fda.gov/drugdisposal.

17 PATIENT COUNSELING INFORMATION

Advise the patient to read the FDA-approved patient labeling (Medication Guide).

Increase in Blood Pressure and Cardiovascular Risk

- Inform patients that Testosterone Undecanoate Capsules can increase blood pressure (BP) which can result in an increase in the risk of major adverse cardiovascular events (MACE), including myocardial infarction, stroke, and cardiovascular death. This risk is greater in patients with established cardiovascular disease or risk factors for cardiovascular disease [see Warnings and Precautions (5.1)].
- Instruct patients about the importance of monitoring BP periodically while on Testosterone Undecanoate Capsules. Instruct patients to report to their healthcare provider the use of concomitant prescription or nonprescription medication, including cough and cold medication which can also increase BP [see Warnings and Precautions (5.3)].

Polycythemia

Advise patients that Testosterone Undecanoate Capsules can cause an increase in hemoglobin/hematocrit levels that may increase the risk of thromboembolic events. Advise patients about the importance of completing laboratory testing as instructed by their health care provider while on Testosterone Undecanoate Capsules [see Warnings and Precautions (5.2)].

Worsening of Benign Prostatic Hyperplasia (BPH) and Potential Risk of Prostate Cancer

Advise patients that Testosterone Undecanoate Capsules can cause increased symptoms of BPH and can increase the risk for prostate cancer. Advise patients to contact their health care provider if they have any prostate-related symptoms [see Warnings and Precautions (5.4)].

Edema

Advise patients that Testosterone Undecanoate Capsules can cause edema in patients with preexisting cardiac, renal, or hepatic disease. Advice patients to notify their health care provider if edema develops or worsens [see Warnings and Precautions (5.10)].

Sleep Apnea

Advise patients that Testosterone Undecanoate Capsules can worsen sleep apnea especially in patients with risk factors such as obesity or chronic lung diseases [see Warnings and Precautions (5.11)].

Gynecomastia

Advise patients that Testosterone Undecanoate Capsules can cause gynecomastia [see Warnings and Precautions (5.12)].

Administration Instructions

Advise patients to take Testosterone Undecanoate Capsules with food [see Dosage and Administration (2.3)].

Distributed By:
Trifluent Pharma, LLC
San Antonio, TX
For more information, call (210) 944-6920

Issued 07/2022
200026767
Rev. 07/22
(testosterone undecanoate) capsules for oral use
CIII

MEDICATION GUIDE
UndecatreIx™ [un-DEK-a-treks]
Testosterone Undecanoate [tes-TOS-ter-one
un-DEK-a-NOE-ate] (testosterone undecanoate)
capsules, for oral use, CII

What is the most important information I should know about Testosterone Undecanoate Capsules?
Testosterone Undecanoate Capsules can cause serious side effects, including:

- Increase in blood pressure.
  - Testosterone Undecanoate Capsules can increase your blood pressure, which can increase your risk of having a heart attack or stroke and can increase your risk of death due to a heart attack or stroke. Your risk may be greater if you have already had a heart attack or stroke or if you have other risk factors for heart attack or stroke.
  - If your blood pressure increases while on Testosterone Undecanoate Capsules, blood pressure medicines may need to be started. If you are taking blood pressure medicines, new blood pressure medicines may need to be added or your current blood pressure medicines may need to be changed to control your blood pressure.
  - If your blood pressure cannot be controlled, Testosterone Undecanoate Capsules may need to be stopped.
  - Your healthcare provider will monitor your blood pressure while you are being treated with Testosterone Undecanoate Capsules.

What are Testosterone Undecanoate Capsules?

- Testosterone Undecanoate Capsules is a prescription medicine that contains testosterone. Testosterone Undecanoate Capsules are used to treat adult men who have low or no testosterone due to certain medical conditions.
- It is not known if Testosterone Undecanoate Capsules are safe or effective in children younger than 18 years old. Improper use of Testosterone Undecanoate Capsules may affect bone growth in children.
- Testosterone Undecanoate is a controlled substance (CIII) because it contains testosterone that can be a target for people who abuse prescription medicines. Keep your Testosterone Undecanoate Capsules in a safe place to protect it. Never give your Testosterone Undecanoate Capsules to anyone else, even if they have the same symptoms you have. Selling or giving away this medicine may harm others and is against the law.
- Testosterone Undecanoate Capsules are not meant for use by women.

Do not take Testosterone Undecanoate Capsules if you:

- have breast cancer.
- have or might have prostate cancer.
- are a woman who is pregnant. Testosterone Undecanoate Capsules may harm your unborn baby.
- are allergic to Testosterone Undecanoate or any ingredients in Testosterone Undecanoate Capsules. See the end of this Medication Guide for a complete list of ingredients in Testosterone Undecanoate Capsules.
- have low testosterone without certain medical conditions. For example, do not take Testosterone Undecanoate Capsules if you have low testosterone due to age.

Before you take Testosterone Undecanoate Capsules, tell your healthcare provider about all of your medical conditions, including if you:

- have high blood pressure or are treated for high blood pressure.
- have a history of diabetes.
- have heart problems.
- have high red blood cell count (hematocrit) or high hemoglobin laboratory value.
- have urinary problems due to an enlarged prostate.
- have liver or kidney problems.
- have problems breathing while you sleep (sleep apnea).

Tell your healthcare provider about all the medicines you take, including prescription and over-the-counter medicines, vitamins, and herbal supplements. Taking Testosterone Undecanoate Capsules with certain other medicines can affect each other. Especially, tell your healthcare provider if you take:

- insulin
- medicines that decrease blood clotting (blood thinners)
- corticosteroids
- medicines that increase blood pressure such as some cold medicine and pain medicines

Know the medicines you take. Ask your healthcare provider or pharmacist for a list of these medicines, if you are not sure. Keep a list of them and show it to your healthcare provider and pharmacist when you get a new medicine.

How should I take Testosterone Undecanoate Capsules?

- Take Testosterone Undecanoate Capsules exactly as your healthcare provider tells you take it.
- Take Testosterone Undecanoate Capsules by mouth 2 times daily. Take 1 time in the morning and take 1 time in the evening. If your dose is 100 mg daily, take 1 time n the morning.
- Take Testosterone Undecanoate Capsules with food.
- Your healthcare provider may change your Testosterone Undecanoate Capsules dose. Do not change your Testosterone Undecanoate Capsules dose without talking to your healthcare provider.

What are the possible side effects of Testosterone Undecanoate?
Testosterone Undecanoate may cause serious side effects including:

- See "What is the most important information I should know about Testosterone Undecanoate Capsules?"
- Increase in red blood cell count (hematocrit) or hemoglobin.
  - Testosterone Undecanoate increases red blood cell counts in some patients. High red blood cell counts increase the risk of blood clots, strokes, and heart attacks.
  - You may need to stop Testosterone Undecanoate if your red blood cell count increases.
  - Your healthcare provider should check your red blood cell count and hemoglobin while you take Testosterone Undecanoate Capsules.
- If you already have an enlarged prostate, your signs and symptoms may worsen while taking Testoster one Undecanoate Capsules.
  - These may include:
  - increased urination at night
  - trouble starting your urine stream
  - urinating many times during the day
  - urge to go to the bathroom right away
  - a urine accident
  - inability to pass urine or weak urine flow
- Increased risk of prostate cancer. Your healthcare provider should check you for prostate cancer or any other prostate problems before you start and while you take Testosterone Undecanoate Capsules.
- Blood clots in the legs or lungs. Signs and symptoms of a blood clot in your leg can include pain, swelling or redness. Signs and symptoms of a blood clot in your lungs can include difficulty breathing or chest pain.
- Abuse. Testosterone can be abused, when taken at higher than prescribed doses and when used with other anabolic androgenic steroids. Abuse can cause serious heart and psychological side effects. Your healthcare provider should check you for signs of abuse before and during treatment with Testosterone Undecanoate Capsules.
- In large doses Testosterone Undecanoate Capsules may lower your sperm count.
- Liver problems. Symptoms of liver problems may include:
  - nausea or vomiting
  - yellowing of your skin or whites of your eyes
  - dark urine
  - pain on the right side of your stomach area (abdominal pain)
- Swelling of your ankles, feet, or body (edema), with or without heart failure.
- Enlarged or painful breasts.
- Breathing problems while you sleep (sleep apnea)

Call your healthcare provider right away if you have any of the serious side effects listed above.
The most common side effect of Testosterone Undecanoate Capsules is high blood pressure.
Other side effects may include headache, joint or back pain, diarrhea, increased red blood cell count, anxiety, constipation, swelling of the legs, and increased prostate specific antigen (PSA) levels.
Tell your healthcare provider if you have any side effect that bothers you or that does not go away.
These are not all the possible side effects of Testosterone Undecanoate Capsules. For more information, ask your healthcare provider or pharmacist.
Call your doctor for medical advice about side effects. You may report side effects to FDA at 1-800-FDA-1088.

How should I store Testosterone Undecanoate Capsules?

- Store Testosterone Undecanoate Capsules at room temperature between 68°F to 77°F (20°C to 25°C).
- Store Testosterone Undecanoate in a dry place.

Keep Testosterone Undecanoate Capsules and all medicines out of the reach of children.
How should I throw away (dispose of) Testosterone Undecanoate Capsules?

- Throw away unused Testosterone Undecanoate Capsules via a take-back option.
- If a take-back option is unavailable, follow FDA instructions at www.fda.gov/drugdisposal for properly throwing away medicine.

General information about the safe and effective use of Testosterone Undecanoate Capsules
Medicines are sometimes prescribed for purposes other than those listed in a Medication Guide. Do not use Testosterone Undecanoate Capsules for a condition for which it was not prescribed. Do not give Testosterone Undecanoate Capsules to other people, even if they have the same symptoms you have. It may harm them. You can ask your pharmacist or healthcare provider for information about Testosterone Undecanoate Capsules that is written for health professionals.

What are the ingredients in Testosterone Undecanoate Capsules?
Active ingredient: testosterone undecanoate
Inactive ingredients: DL-alpha-tocopheryl acetate (Vitamin E), phytosterol esters, polyoxyl 40 hydrogenated castor oil and propylene glycol monolaurate. The ingredients of the gelatin capsule shells are gelatin, glycerin, purified water, sorbitol, and titanium dioxide.
Distributed By:
Trifluent Pharma,LLC
San Antonio, TX 78213
For more information, call 210-944-6920

This Medication Guide has been approved by the U.S. Food and Drug Administration.

Issued: 09/2022

PRINCIPAL DISPLAY PANEL - 200 mg Capsule Bottle Label

TRIFLUENT
PHARMA™

NDC 73352-105-22

Undecatrex™

CIII

(Testosterone Undecanoate)
Capsules

200 mg

Dispense with attached
Medication Guide to
each patient

Rx only

120 Capsules